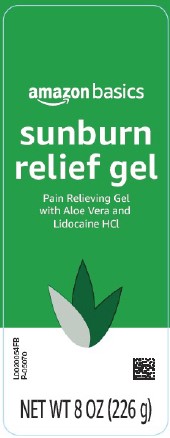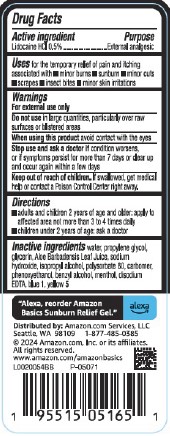 DRUG LABEL: Sunburn Relief Gel
NDC: 72288-005 | Form: GEL
Manufacturer: Amazon.com Services LLC
Category: otc | Type: HUMAN OTC DRUG LABEL
Date: 20250627

ACTIVE INGREDIENTS: LIDOCAINE HYDROCHLORIDE 5 mg/1 g
INACTIVE INGREDIENTS: WATER; PROPYLENE GLYCOL; GLYCERIN; ALOE VERA LEAF; SODIUM HYDROXIDE; ISOPROPYL ALCOHOL; POLYSORBATE 80; CARBOMER HOMOPOLYMER, UNSPECIFIED TYPE; PHENOXYETHANOL; BENZYL ALCOHOL; MENTHOL; EDETATE DISODIUM; FD&C BLUE NO. 1; FD&C YELLOW NO. 5

Basics 005.003/005AE
Sunburn Relief Gel

Active ingredient

Lidocaine HCl 0.5%

Purpose

External analgesic

Uses

for the temporary relief of pain and itching associated with

- minor burns
- sunburn
- minor cuts
- scrapes
- insect bites
- minor skin irritations

Warnings

For external use only

Do not use

in large quantities, particularly over raw surfaces or blistered areas

When using this product

avoid contact with the eyes

Stop use and ask a doctor if

condition worsens, or if symptoms persist for more than 7 days or clear up and occur again within a few days

Keep out of reach of children.

If swallowed, get medical help or contact a Poison Control Center right away.

Directions

- adults and children 2 years of age and older: apply to affected area not more than 3 to 4 times daily
- children under 2 years of age: ask a doctor

Inactive ingredients

water, propylene glycol, glycerin, Aloe Barbadensis Leaf Juice, sodium hydroxide, isopropyl alcohol, polysorbate 80, carbomer, phenoxyethanol, benzyl alcohol, menthol, disodium EDTA, blue 1, yellow 5

Adverse reaction

"Alexa, reorder Amazon Basics Sunburn Relief Gel." alexa

Distributed by: Amazon.com Services LLC

Seattle, WA 98109 1-877-485-0385

©2024 Amazon.com Services, LLC. or its affiliates

www.amazon.com/amazonbasics

Principl display panel

amazon basics

sunburn relief gel

Pain Relieving Gel

with Aloe Vera and Lidocaine HCl

NET WT 8 OZ (226 g)